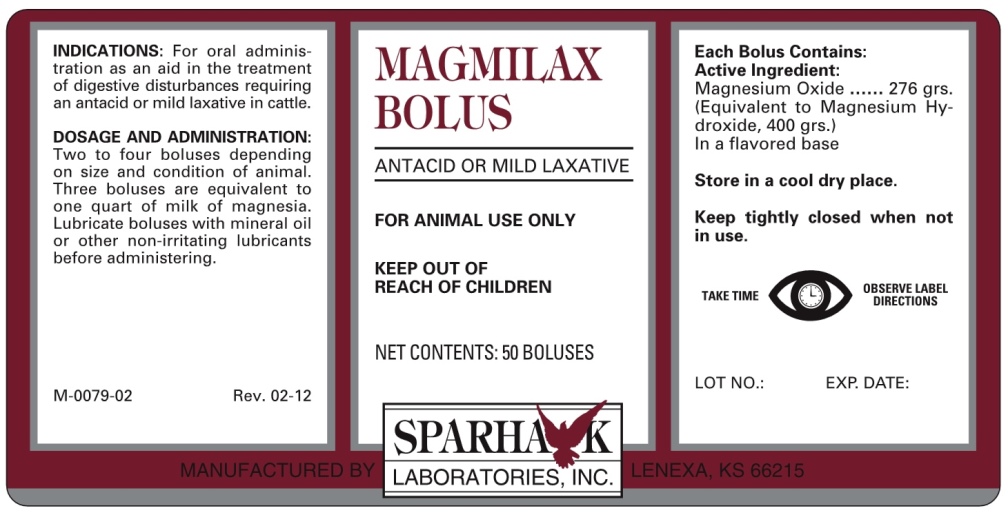 DRUG LABEL: MAGMILAX BOLUS
NDC: 58005-079 | Form: TABLET
Manufacturer: Sparhawk Laboratories, Inc.
Category: animal | Type: OTC ANIMAL DRUG LABEL
Date: 20140429

ACTIVE INGREDIENTS: MAGNESIUM OXIDE 276 g/1 1

MAGMILAX BOLUS

INDICATIONS AND USAGE

ANTIACID OR MILD LAXATIVE

FOR ANIMAL USE ONLY

KEEP OUT OF REACH OF CHILDREN

INDICATIONS

For oral administration as an aid in the treatment of digestive disturbances requiring an antacid or mild laxative in cattle.

DOSAGE AND ADMINISTRATION

Two to four boluses depending on size and condition of animal. Three boluses are equivalent to one quart of milk of magnesia. Lubricate boluses with mineral oil or other non-irritating lubricants before administering.

COMPONENTS

Each Bolus Contains:
Active Ingredient:
Magnesium Oxide ...... 276 grs.
(Equivalent to Magnesium Hydroxide, 400 grs.)
In a flavored base.

STORAGE AND HANDLING

Store in a cool dry place.;Keep tightly closed when not in use.

TAKE TIME TO OBSERVE LABEL DIRECTIONS